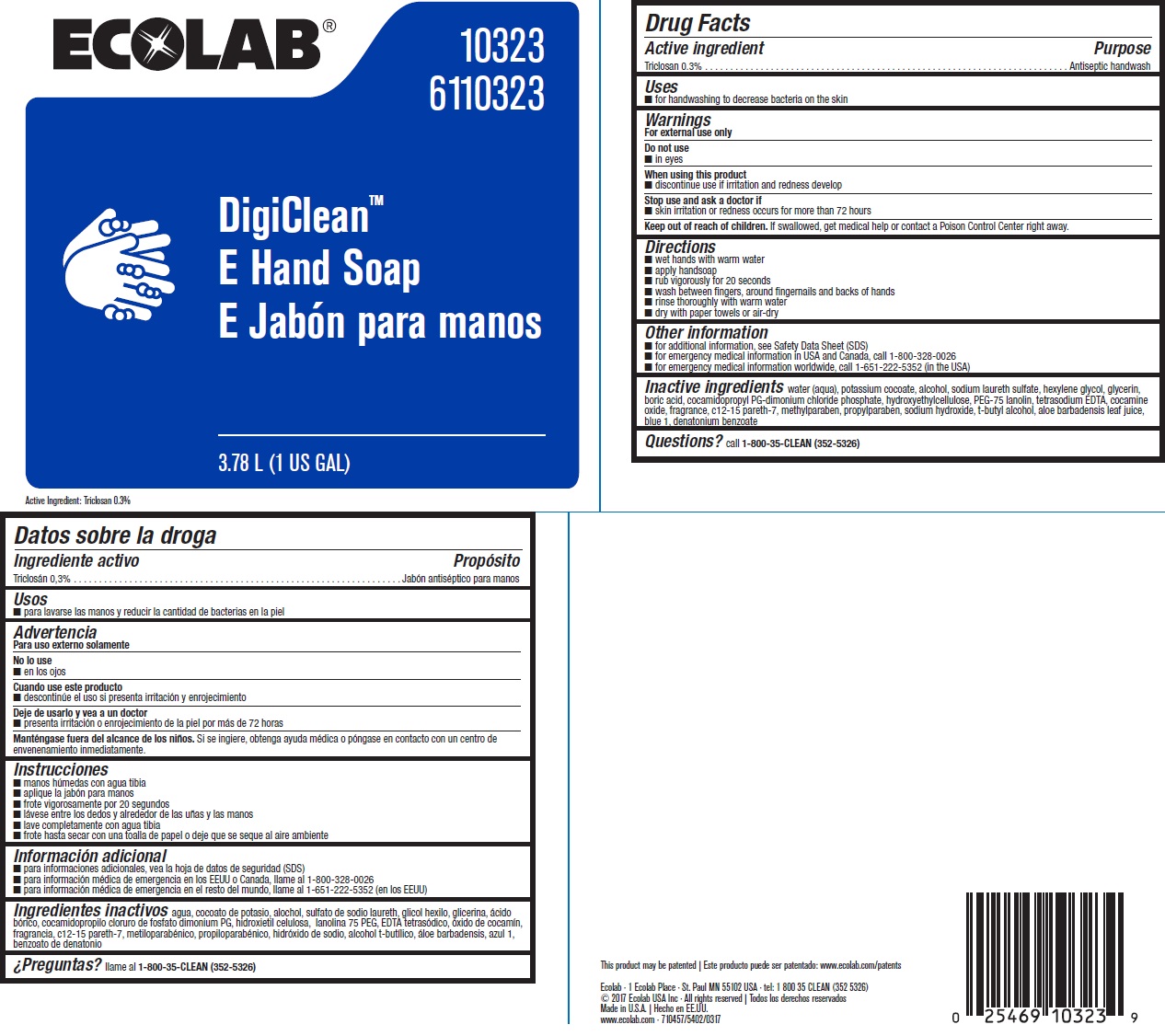 DRUG LABEL: DigiClean E
NDC: 47593-305 | Form: SOLUTION
Manufacturer: Ecolab Inc.
Category: otc | Type: HUMAN OTC DRUG LABEL
Date: 20240314

ACTIVE INGREDIENTS: Triclosan 3 mg/1 mL
INACTIVE INGREDIENTS: WATER; POTASSIUM COCOATE; SODIUM LAURETH SULFATE; ALCOHOL; HEXYLENE GLYCOL; BORIC ACID; HYDROXYETHYL CELLULOSE (3000 MPA.S AT 1%); COCAMIDOPROPYL PG-DIMONIUM CHLORIDE PHOSPHATE; EDETATE SODIUM; PEG-75 LANOLIN; COCAMINE OXIDE; METHYLPARABEN; PROPYLPARABEN; ALOE VERA LEAF; FD&C BLUE NO. 1

Drug Facts

Active ingredient

Triclosan, 0.3%

Purpose

Antiseptic handwash

Uses

- for handwashing to decrease bacteria on the skin

Warnings

For external use only

Do not use

- in eyes

When using this product

discontinue use if irritation and redness develop

Stop use and ask a doctor if

- skin irritation or redness occurs for more than 72 hours

Keep out of reach of children. If swallowed, get medical help or contact a Poison Control Center right away.

Directions

- Wet hands with warm water
- Apply handsoap
- Rub vigorously for 20 seconds
- Wash between fingers, around fingernails and backs of hands
- Rinse thoroughly with warm water
- Dry with paper towels or air-dry

Other information

- For additional information, see Safety Data Sheet (SDS)
- For emergency medical information in USA and Canada, call 1-800-328-0026
- For emergency medical information worldwide, call 1-651-222-5352 (in the USA)

INACTIVE INGREDIENT

Inactive ingredientswater (aqua), potassium cocoate, alcohol, sodium laureth sulfate, hexylene glycol, glycerin, boric acid, cocamidopropyl PG-dimonium chloride phosphate, hydroxyethylcellulose, PEG-75 lanolin, tetrasodium EDTA, cocamine oxide, fragrance, c12-15 pareth-7, methylparaben, propylparaben, sodium hydroxide, t-butyl alcohol, aloe barbadensis leaf juice, blue 1, denatonium benzoate

Questions? Call 1-800-35-CLEAN (352-5326)

Principal display panel/Representative label

ECOLAB

10323

6110323

DigiClean™

E Hand Soap

3.78 L (1 US GAL)

This product may be patented: www.ecolab.com/patents

Ecolab · 1 Ecolab Place · St. Paul MN 55102 USA · tel: 1 800 35 CLEAN (352 5326)

© 2017 Ecolab USA Inc · All rights reserved

Made in U.S.A.

www.ecolab.com · 710457/5402/0317